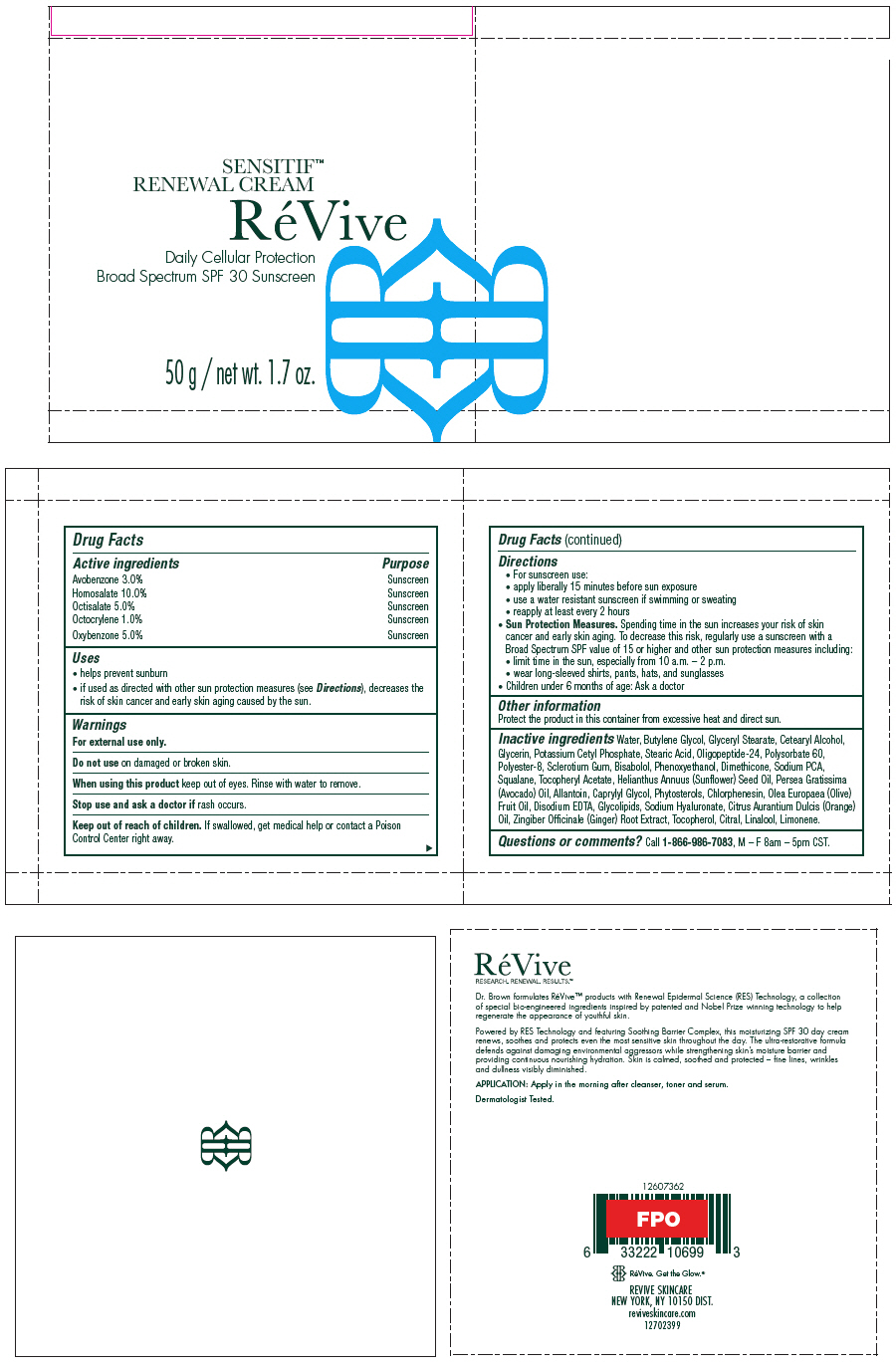 DRUG LABEL: ReVive Sensitif Renewal 
NDC: 58411-419 | Form: CREAM
Manufacturer: RéVive Skincare
Category: otc | Type: HUMAN OTC DRUG LABEL
Date: 20180118

ACTIVE INGREDIENTS: AVOBENZONE 30 mg/1 g; HOMOSALATE 100 mg/1 g; OCTISALATE 50 mg/1 g; OCTOCRYLENE 10 mg/1 g; OXYBENZONE 50 mg/1 g
INACTIVE INGREDIENTS: WATER; BUTYLENE GLYCOL; GLYCERYL MONOSTEARATE; CETOSTEARYL ALCOHOL; GLYCERIN; POTASSIUM CETYL PHOSPHATE; STEARIC ACID; POLYSORBATE 60; POLYESTER-8 (1400 MW, CYANODIPHENYLPROPENOYL CAPPED); BETASIZOFIRAN; LEVOMENOL; PHENOXYETHANOL; DIMETHICONE; SODIUM PYRROLIDONE CARBOXYLATE; SQUALANE; .ALPHA.-TOCOPHEROL ACETATE; SUNFLOWER OIL; AVOCADO OIL; ALLANTOIN; CAPRYLYL GLYCOL; CHLORPHENESIN; OLIVE OIL; EDETATE DISODIUM ANHYDROUS; HYALURONATE SODIUM; ORANGE OIL; GINGER; TOCOPHEROL; CITRAL; LINALOOL, (+/-)-; LIMONENE, (+)-

RéVive Sensitif™ Renewal
Cream Daily Cellular Protection Broad Spectrum SPF 30 Sunscreen

Drug Facts

ACTIVE INGREDIENT

Active ingredients | Purpose
Avobenzone 3.0% | Sunscreen
Homosalate 10.0% | Sunscreen
Octisalate 5.0% | Sunscreen
Octocrylene 1.0% | Sunscreen
Oxybenzone 5.0% | Sunscreen

Uses

- helps prevent sunburn
- if used as directed with other sun protection measures (see Directions), decreases the risk of skin cancer and early skin aging caused by the sun.

Warnings

For external use only.

Do not use on damaged or broken skin.

When using this product keep out of eyes. Rinse with water to remove.

Stop use and ask a doctor if rash occurs.

Keep out of reach of children. If swallowed, get medical help or contact a Poison Control Center right away.

Directions

-
  - For sunscreen use:
  - apply liberally 15 minutes before sun exposure
  - use a water resistant sunscreen if swimming or sweating
  - reapply at least every 2 hours
- Sun Protection Measures. Spending time in the sun increases your risk of skin cancer and early skin aging. To decrease this risk, regularly use a sunscreen with a Broad Spectrum SPF value of 15 or higher and other sun protection measures including:
  - limit time in the sun, especially from 10 a.m. – 2 p.m.
  - wear long-sleeved shirts, pants, hats, and sunglasses
- Children under 6 months of age: Ask a doctor

Other information

Protect the product in this container from excessive heat and direct sun.

Inactive ingredients

Water, Butylene Glycol, Glyceryl Stearate, Cetearyl Alcohol, Glycerin, Potassium Cetyl Phosphate, Stearic Acid, Oligopeptide-24, Polysorbate 60, Polyester-8, Sclerotium Gum, Bisabolol, Phenoxyethanol, Dimethicone, Sodium PCA, Squalane, Tocopheryl Acetate, Helianthus Annuus (Sunflower) Seed Oil, Persea Gratissima (Avocado) Oil, Allantoin, Caprylyl Glycol, Phytosterols, Chlorphenesin, Olea Europaea (Olive) Fruit Oil, Disodium EDTA, Glycolipids, Sodium Hyaluronate, Citrus Aurantium Dulcis (Orange) Oil, Zingiber Officinale (Ginger) Root Extract, Tocopherol, Citral, Linalool, Limonene.

Questions or comments?

Call 1-866-986-7083, M – F 8am – 5pm CST.

PRINCIPAL DISPLAY PANEL - 50 g Jar Carton

SENSITIF™
RENEWAL CREAM

RéVive

Daily Cellular Protection
Broad Spectrum SPF 30 Sunscreen

50 g / net wt. 1.7 oz.